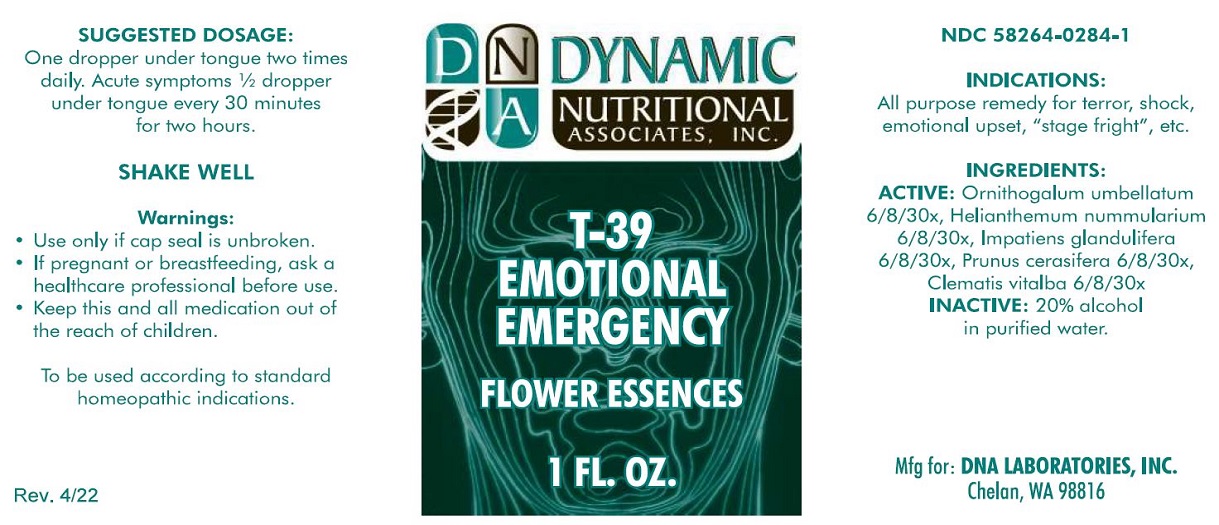 DRUG LABEL: T-39
NDC: 58264-0284 | Form: SOLUTION
Manufacturer: DNA Labs, Inc.
Category: homeopathic | Type: HUMAN OTC DRUG LABEL
Date: 20250109

ACTIVE INGREDIENTS: ORNITHOGALUM UMBELLATUM 30 [hp_X]/1 mL; HELIANTHEMUM NUMMULARIUM WHOLE 30 [hp_X]/1 mL; IMPATIENS GLANDULIFERA WHOLE 30 [hp_X]/1 mL; PRUNUS CERASIFERA WHOLE 30 [hp_X]/1 mL; CLEMATIS VITALBA WHOLE 30 [hp_X]/1 mL
INACTIVE INGREDIENTS: ALCOHOL; WATER

T-39

NDC 58264-0284-1

INDICATIONS

PURPOSE

All purpose remedy for terror, shock, emotional upset, "stage fright", etc.

INGREDIENTS

INACTIVE INGREDIENT

Ornithogalum umbellatum 6/8/30x, Helianthemum nummularium 6/8/30x, Impatiens glandulifera 6/8/30x, Prunus cerasifera 6/8/30x, Clematis vitalba 6/8/30x, 20% alcohol in purified water.

SUGGESTED DOSAGE

One dropper under tongue two times daily. Acute symptoms ½ dropper under tongue every 30 minutes for two hours.

STORAGE AND HANDLING

SHAKE WELL

Warnings

- Use only if cap seal is unbroken.

PREGNANCY OR BREAST FEEDING

- As with drugs if you are pregnant or nursing a baby seek professional advice before using this product.

KEEP OUT OF REACH OF CHILDREN

- Keep this and all medication out of the reach of children.

To be used according to standard homeopathic indications.

PRINCIPAL DISPLAY PANEL - 1 FL. OZ. Bottle Label

DYNAMIC
NUTRITIONAL
ASSOCIATES, INC.

T-39

EMOTIONAL
EMERGENCY

FLOWER ESSENCES

1 FL. OZ.